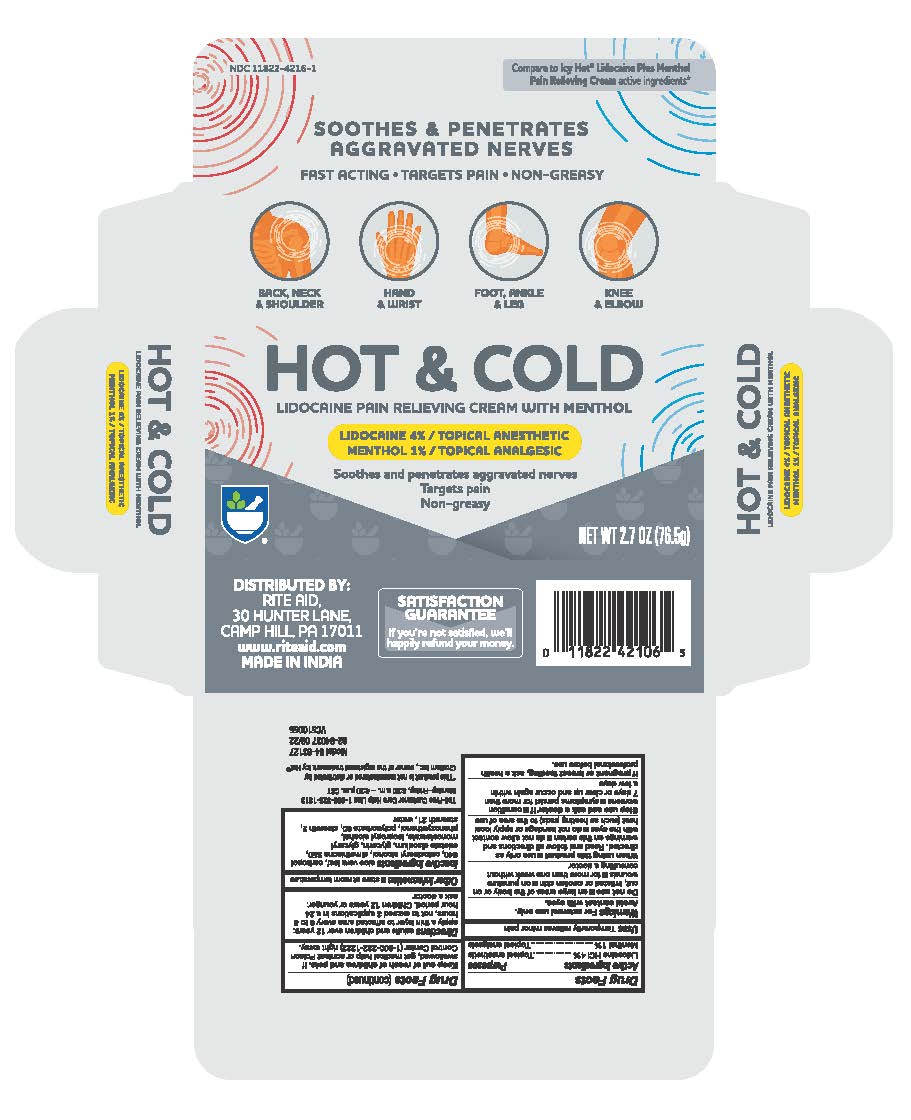 DRUG LABEL: Rite Aid Hot and Cold Pain Relief
NDC: 11822-4216 | Form: CREAM
Manufacturer: Rite Aid
Category: otc | Type: HUMAN OTC DRUG LABEL
Date: 20241218

ACTIVE INGREDIENTS: LIDOCAINE 0.4 g/1 g; MENTHOL 0.1 g/1 g
INACTIVE INGREDIENTS: ALOE VERA LEAF; CARBOMER 940; DIMETHICONE 350; CETOSTEARYL ALCOHOL; GLYCERIN; ISOPROPYL ALCOHOL; PHENOXYETHANOL; EDETATE DISODIUM; STEARETH-2; GLYCERYL MONOSTEARATE; POLYSORBATE 60; STEARETH-21; WATER

Rite Aid Hot & Cold Pain Relief Cream

Rite Aid Lidocaine-Menthol Pain Relief Cream

Active Ingredients

Lidocaine HCl 4%

Menthol 1%

Purposes

Topical anesthetic

Uses

Temporarily relieves minor pain

Warnings

For external use only

Avoid contact with eyes

Do not use

- on large areas of the body or on cut, irritated or swollen skin
- on puncture wounds
- for more than one week without consulting a doctor

When using this product

- Use only as directed. Read and follow all directions and warnings on this carton.
- do not allow contact with eyes

- do not bandage or apply local heat (such as heating pads) to the area of use

Stop use and ask a doctor if

- condition worsens
- symptoms persist for more than 7 days or clear up and occur again within a few days

If pregnant or breast-feeding,

ask a health professional before use.

Keep out of reach of children and pets.

If swallowed, get medical help or contact a Poison Control Center (1-800-222-1222) right away.

Directions

adults and children over 12 years:

- apply a thin layer to affected area every 6 to 8 hours, not to exceed 3 applications in a 24 hour period

children 12 years or younger: ask a doctor

Inactive ingredients

aloe vera leaf, carbopol 940, cetostearyl alcohol, dimethicone 350, edetate disodium, glycerin, glyceryl monostearate, isopropyl alcohol, phenoxyethanol, polysorbate 60, steareth 2, steareth 21, water